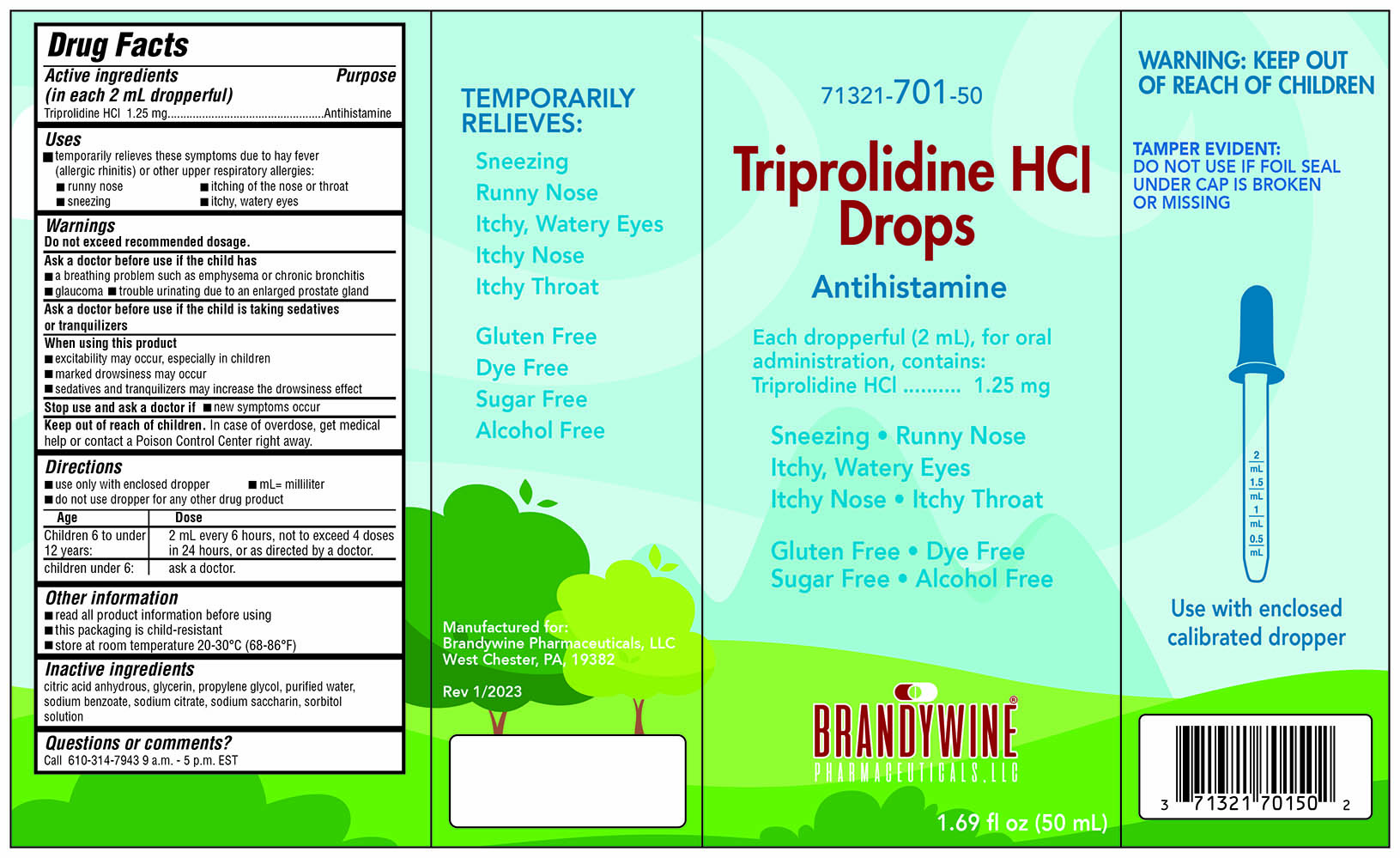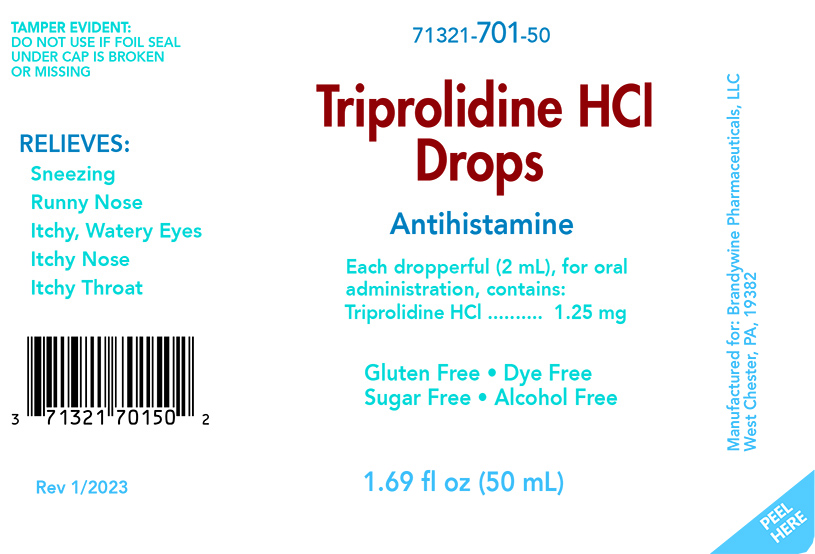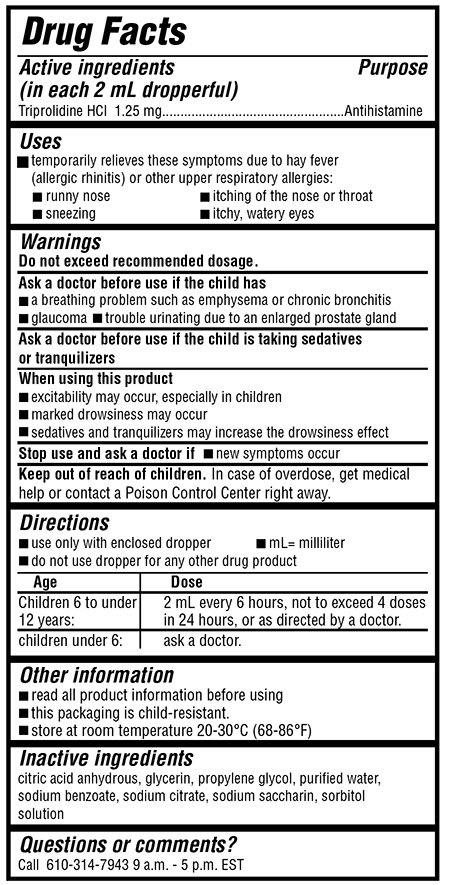 DRUG LABEL: Triprolidine HCl Drops
NDC: 71321-701 | Form: LIQUID
Manufacturer: Brandywine Pharmaceuticals, LLC
Category: otc | Type: HUMAN OTC DRUG LABEL
Date: 20240108

ACTIVE INGREDIENTS: TRIPROLIDINE HYDROCHLORIDE 1.25 mg/2 mL
INACTIVE INGREDIENTS: ANHYDROUS CITRIC ACID; GLYCERIN; PROPYLENE GLYCOL; WATER; SODIUM BENZOATE; SODIUM CITRATE; SACCHARIN SODIUM; SORBITOL

Triprolidine HCl Drops

Triprolidine HCl Drops

NDC 71321-701-50

Active ingredients (in each 2 mL)

Triprolidine HCI 1.25 mg

Purpose

Antihistamine

Uses

■ temporarily relieves these symptoms due to hay fever

(allergic rhinitis) or other upper respiratory allergies:

■ runny nose ■ itching of the nose or throat

■ sneezing ■ itchy, watery eyes

Warnings

Do not exceed recommended dosage.

Ask a doctor before use if the child has

■ a breathing problem such as emphysema or chronic bronchitis

■ glaucoma

■ trouble urinating due to an enlarged prostate

Ask a doctor before use if the child is

taking sedatives or tranquilizers

When using this product

■ excitability may occur, especially in children

■ marked drowsiness may occur

■ sedatives and tranquilizers may increase the drowsiness effect

Stop use and ask a doctor if

■ new symptoms occur

Keep out of reach of children.

In case of overdose, get medical help or contact a Poison Control Center right away.

Directions

■ use only with enclosed dropper ■ mL= milliliter

■ do not use dropper for any other drug product

children 6 to under 12 years: 2 mL every 6 hours, not to exceed 4 doses in 24 hours, or as directed by a doctor.

children under 6: ask a doctor.

Directions

■ use only with enclosed dropper ■ mL= milliliter

■ do not use dropper for any other drug product

children 6 to under 12 years: 2 mL every 6 hours, not to exceed 4 doses in 24 hours, or as directed by a doctor.

children under 6: ask a doctor.

Other information

■ read all product information before using

■ this packaging is child-resistant.

■ store at room temperature 20-30°C (68-86°F)

Inactive ingredients

citric acid anhydrous, glycerin, propylene glycol, purified water, sodium benzoate, sodium citrate, sodium saccharin, sorbitol solution

Questions or comments?

Call 610-314-7943 9 a.m. - 5 p.m. EST.

PRINCIPAL DISPLAY PANEL

NDC 71321-701-50
Triprolidine HCl Drops
1.69 fl oz (50 mL)